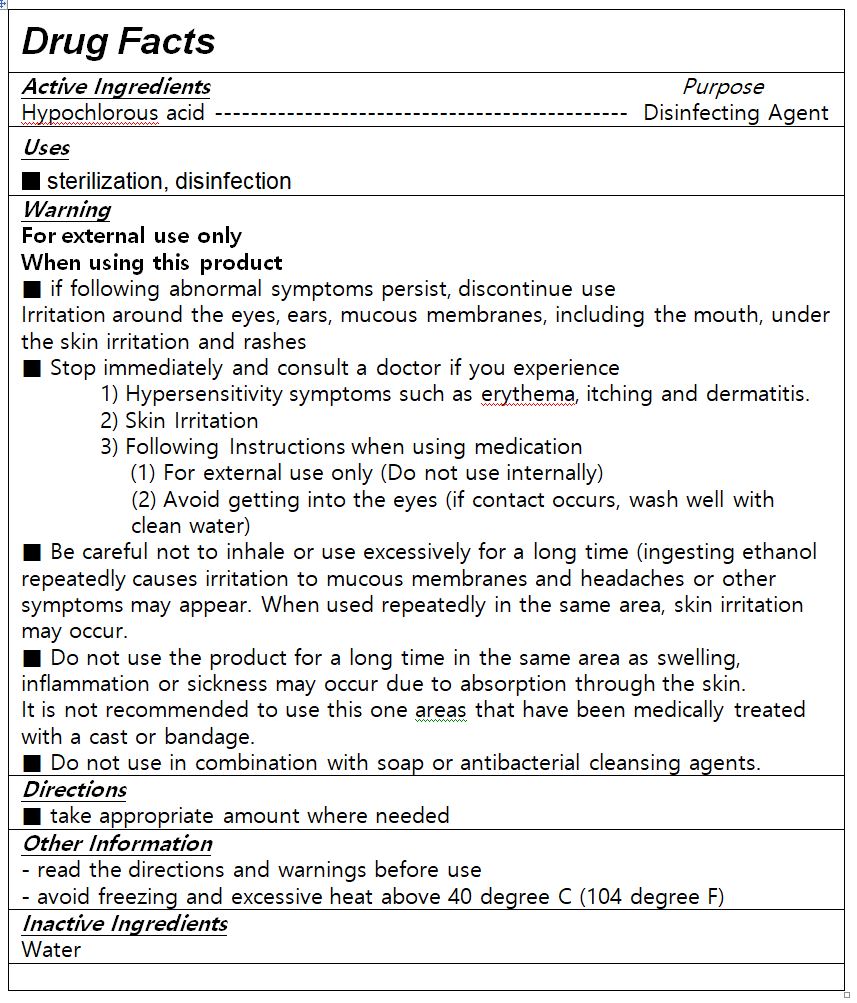 DRUG LABEL: PURO MEDI
NDC: 81128-0001 | Form: LIQUID
Manufacturer: The Garnet Co., Ltd.
Category: otc | Type: HUMAN OTC DRUG LABEL
Date: 20201122

ACTIVE INGREDIENTS: HYPOCHLOROUS ACID 0.003 g/100 mL
INACTIVE INGREDIENTS: WATER

Drug Facts

ACTIVE INGREDIENT

Hypochlorous Acid

INACTIVE INGREDIENT

WATER

PURPOSE

sterilization, disinfection

KEEP OUT OF REACH OF THE CHILDREN

INDICATIONS AND USAGE

Apply an appropriate amount on your hands and rub well to dry.

WARNINGS

1. Do not use on the following body parts. A wide range of body parts and damaged skin around the eyes and ears, in the oral cavity (may have irritating effects)
2. If the following symptoms appear, stop using them immediately and consult a doctor or pharmacist.
1) Hypersensitivity symptoms such as rash, erythema, itching, and edema
2) Skin irritation symptoms

DOSAGE AND ADMINISTRATION

for external use only